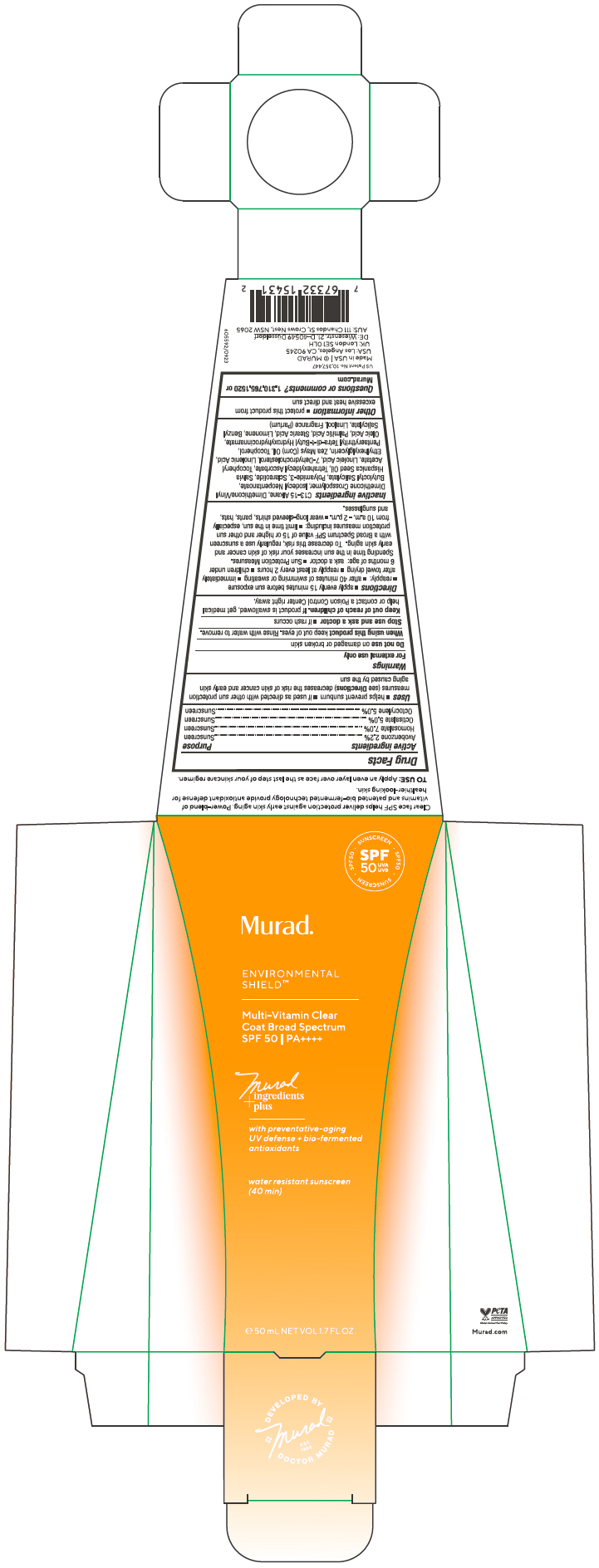 DRUG LABEL: Multi Vitamin Clear Coat Broad Spectrum
NDC: 70381-125 | Form: GEL
Manufacturer: Murad, LLC
Category: otc | Type: HUMAN OTC DRUG LABEL
Date: 20250110

ACTIVE INGREDIENTS: AVOBENZONE 2.2 g/100 mL; HOMOSALATE 7 g/100 mL; OCTISALATE 5 g/100 mL; OCTOCRYLENE 5 g/100 mL
INACTIVE INGREDIENTS: C13-15 ALKANE; DIMETHICONE/VINYL DIMETHICONE CROSSPOLYMER (SOFT PARTICLE); ISODECYL NEOPENTANOATE; BUTYLOCTYL SALICYLATE; POLYAMIDE-3 (30000 MW); SCLAREOLIDE; CHIA SEED OIL; TETRAHEXYLDECYL ASCORBATE; .ALPHA.-TOCOPHEROL ACETATE; LINOLEIC ACID; 7-DEHYDROCHOLESTEROL; LINOLENIC ACID; ETHYLHEXYLGLYCERIN; CORN OIL; TOCOPHEROL; PENTAERYTHRITOL TETRAKIS(3-(3,5-DI-TERT-BUTYL-4-HYDROXYPHENYL)PROPIONATE); OLEIC ACID; PALMITIC ACID; STEARIC ACID; LIMONENE, (+)-; BENZYL SALICYLATE; LINALOOL, (+/-)-

Multi-Vitamin Clear Coat Broad Spectrum
SPF 50

Drug Facts

ACTIVE INGREDIENT

Active ingredients | Purpose
Avobenzone 2.2% | Sunscreen
Homosalate 7.0% | Sunscreen
Octisalate 5.0% | Sunscreen
Octocrylene 5.0% | Sunscreen

Uses

- helps prevent sunburn
- if used as directed with other sun protection measures (see Directions) decreases the risk of skin cancer and early skin aging caused by the sun

Warnings

For external use only

Do not use on damaged or broken skin

When using this product keep out of eyes. Rinse with water to remove.

Stop use and ask a doctor

- if rash occurs

Keep out of reach of children. If product is swallowed, get medical help or contact a Poison Control Center right away.

Directions

- apply evenly 15 minutes before sun exposure
- reapply:
  - after 40 minutes of swimming or sweating
  - immediately after towel drying
  - reapply at least every 2 hours
- children under 6 months of age: ask a doctor
- Sun Protection Measures. Spending time in the sun increases your risk of skin cancer and early skin aging. To decrease this risk, regularly use a sunscreen with a Broad Spectrum SPF value of 15 or higher and other sun protection measures including:
  - limit time in the sun, especially from 10 a.m. - 2 p.m.
  - wear long-sleeved shirts, pants, hats, and sunglasses.

Inactive ingredients

C13-15 Alkane, Dimethicone/Vinyl Dimethicone Crosspolymer, Isodecyl Neopentanoate, Butyloctyl Salicylate, Polyamide-3, Sclareolide, Salvia Hispanica Seed Oil, Tetrahexyldecyl Ascorbate, Tocopheryl Acetate, Linoleic Acid, 7-Dehydrocholesterol, Linolenic Acid, Ethylhexylglycerin, Zea Mays (Corn) Oil, Tocopherol, Pentaerythrityl Tetra-di-t-Butyl Hydroxyhydrocinnamate, Oleic Acid, Palmitic Acid, Stearic Acid, Limonene, Benzyl Salicylate, Linalool, Fragrance (Parfum)

Other information

- protect this product from excessive heat and direct sun

Questions or comments?

1.310.765.1520 or Murad.com

PRINCIPAL DISPLAY PANEL - 50 mL Tube Carton

SPF
50
UVA
UVB

SUNSCREEN • SPF50 • SUNSCREEN • SPF50 •

Murad®

ENVIRONMENTAL
SHIELD™

Multi-Vitamin Clear
Coat Broad Spectrum
SPF 50 | PA++++

Murad
ingredients
plus

with preventative-aging
UV defense + bio-fermented
antioxidants

water resistant sunscreen
(40 min)

℮ 50 mL NET VOL 1.7 FL OZ